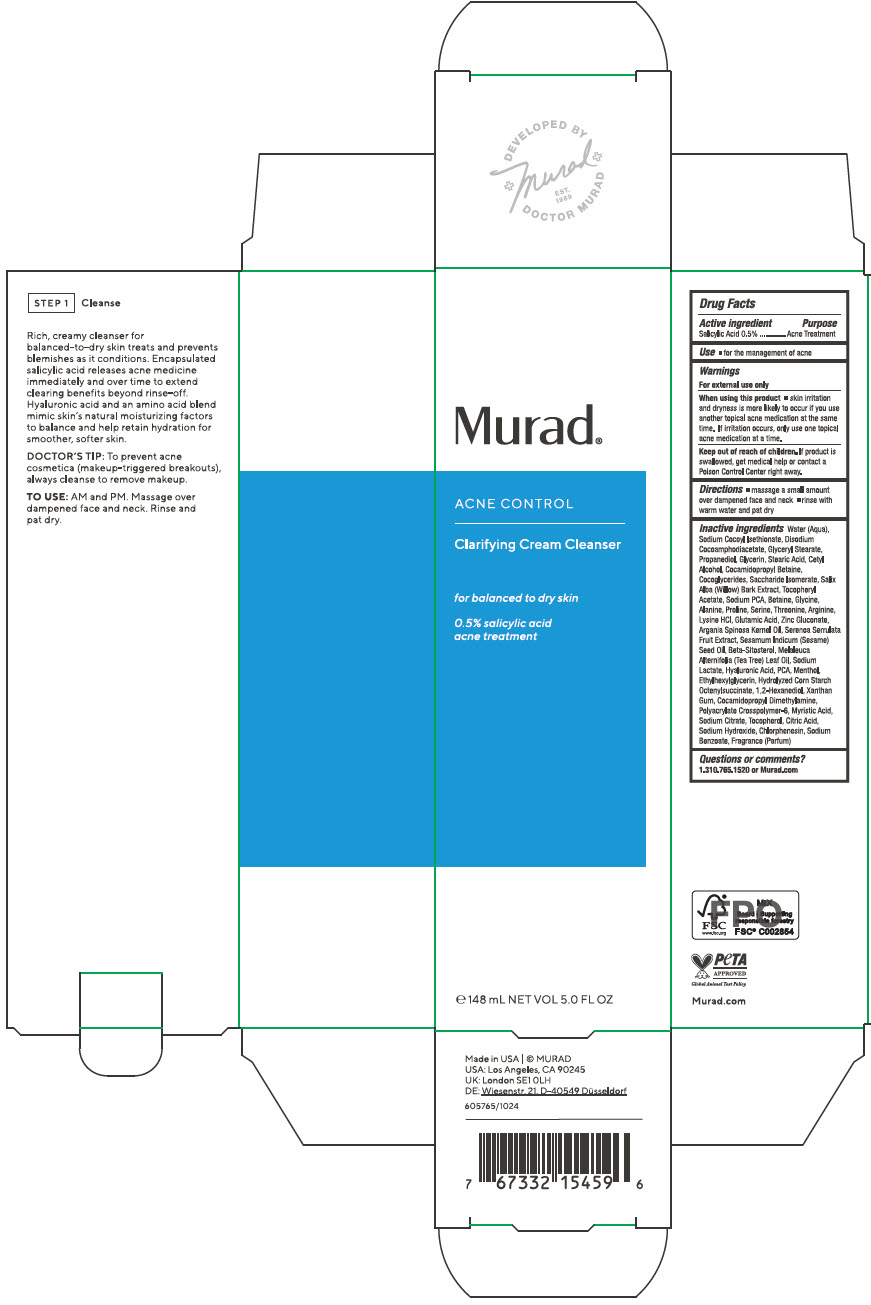 DRUG LABEL: Clarifying Cleanser
NDC: 70381-128 | Form: SOLUTION
Manufacturer: Murad, LLC
Category: otc | Type: HUMAN OTC DRUG LABEL
Date: 20250328

ACTIVE INGREDIENTS: SALICYLIC ACID 0.5 g/100 mL
INACTIVE INGREDIENTS: WATER; SODIUM COCOYL ISETHIONATE; DISODIUM COCOAMPHODIACETATE; GLYCERYL MONOSTEARATE; PROPANEDIOL; GLYCERIN; STEARIC ACID; CETYL ALCOHOL; COCAMIDOPROPYL BETAINE; COCO-GLYCERIDES; SACCHARIDE ISOMERATE; SALIX ALBA BARK; .ALPHA.-TOCOPHEROL ACETATE; SODIUM PYRROLIDONE CARBOXYLATE; BETAINE; GLYCINE; ALANINE; PROLINE; SERINE; THREONINE; ARGININE; LYSINE HYDROCHLORIDE; GLUTAMIC ACID; ZINC GLUCONATE; ARGAN OIL; SAW PALMETTO; SESAME OIL; .BETA.-SITOSTEROL; TEA TREE OIL; SODIUM LACTATE; HYALURONIC ACID; PIDOLIC ACID; MENTHOL, UNSPECIFIED FORM; ETHYLHEXYLGLYCERIN; STARCH, CORN; OCTENYLSUCCINIC ACID; 1,2-HEXANEDIOL; XANTHAN GUM; COCAMIDOPROPYL DIMETHYLAMINE; AMMONIUM ACRYLOYLDIMETHYLTAURATE, DIMETHYLACRYLAMIDE, LAURYL METHACRYLATE AND LAURETH-4 METHACRYLATE COPOLYMER, TRIMETHYLOLPROPANE TRIACRYLATE CROSSLINKED (45000 MPA.S); MYRISTIC ACID; SODIUM CITRATE, UNSPECIFIED FORM; TOCOPHEROL; CITRIC ACID MONOHYDRATE; SODIUM HYDROXIDE; CHLORPHENESIN; SODIUM BENZOATE

Clarifying Cream Cleanser

Drug Facts

Active ingredients

Salicylic Acid 0.5%

Purpose

Acne Treatment

Use

- for the management of acne

Warnings

For external use only

When using this product

- skin irritation and dryness is more likely to occur if you use another topical acne medication at the same time. If irritation occurs, only use one topical acne medication at a time.

Keep out of reach of children. If product is swallowed, get medical help or contact a Poison Control Center right away.

Directions

- massage a small amount over dampened face and neck
- rinse with warm water and pat dry

Inactive ingredients

Water (Aqua), Sodium Cocoyl Isethionate, Disodium Cocoamphodiacetate, Glyceryl Stearate, Propanediol, Glycerin, Stearic Acid, Cetyl Alcohol, Cocamidopropyl Betaine, Cocoglycerides, Saccharide Isomerate, Salix Alba (Willow) Bark Extract, Tocopheryl Acetate, Sodium PCA, Betaine, Glycine, Alanine, Proline, Serine, Threonine, Arginine, Lysine HCl, Glutamic Acid, Zinc Gluconate, Argania Spinosa Kernel Oil, Serenoa Serrulata Fruit Extract, Sesamum Indicum (Sesame) Seed Oil, Beta-Sitosterol, Melaleuca Alternifolia (Tea Tree) Leaf Oil, Sodium Lactate, Hyaluronic Acid, PCA, Menthol, Ethylhexylglycerin, Hydrolyzed Corn Starch Octenylsuccinate, 1,2-Hexanediol, Xanthan Gum, Cocamidopropyl Dimethylamine, Polyacrylate Crosspolymer-6, Myristic Acid, Sodium Citrate, Tocopherol, Citric Acid, Sodium Hydroxide, Chlorphenesin, Sodium Benzoate, Fragrance (Parfum)

Questions or comments?

1.310.765.1520 or Murad.com

PRINCIPAL DISPLAY PANEL - 148 mL Tube Carton

Murad®

ACNE CONTROL

Clarifying Cream Cleanser

for balanced to dry skin

0.5% salicylic acid
acne treatment

℮ 148 mL NET VOL 5.0 FL OZ